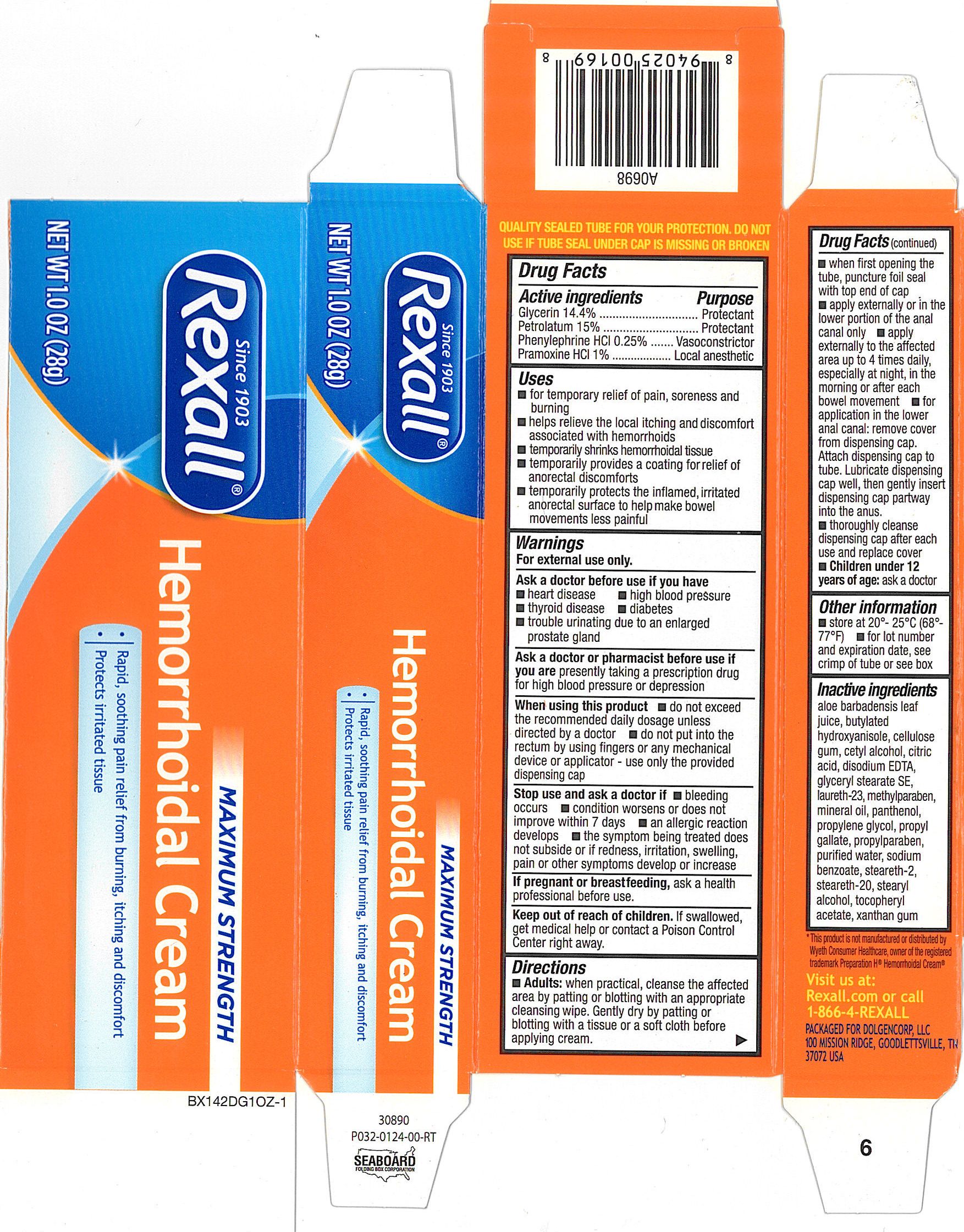 DRUG LABEL: Rexall Maximum Strength Hemorrhoidal
NDC: 55910-402 | Form: CREAM
Manufacturer: Dolgencorp, Inc.
Category: otc | Type: HUMAN OTC DRUG LABEL
Date: 20110628

ACTIVE INGREDIENTS: PRAMOXINE HYDROCHLORIDE 10 mg/1 g; GLYCERIN 144 mg/1 g; PETROLATUM 150 mg/1 g; PHENYLEPHRINE HYDROCHLORIDE 2.5 mg/1 g
INACTIVE INGREDIENTS: WATER; CETYL ALCOHOL; GLYCERYL MONOSTEARATE; CARBOXYMETHYLCELLULOSE SODIUM; LAURETH-23; MINERAL OIL; PANTHENOL; PROPYL GALLATE; STEARYL ALCOHOL; PROPYLENE GLYCOL; SODIUM BENZOATE; STEARETH-2; STEARETH-20; .ALPHA.-TOCOPHEROL ACETATE, D-; XANTHAN GUM; ALOE VERA LEAF; BUTYLATED HYDROXYANISOLE; EDETATE DISODIUM; CITRIC ACID MONOHYDRATE; METHYLPARABEN; PROPYLPARABEN

drug facts

Active ingredients Purpose
Glycerin 14.4%.................................................Protectant
Petrolatum 15%...............................................Protectant
Phenylephrine Hydrochloride 0.25%...................Vasoconstrictor
Pramoxine HCl 1%...........................................Local anesthetic

Uses
- for temporary relief of pain, soreness and burning
- helps relieve the local itching and discomfort associated with hemorrhoids
- temporarily shrinks hemorrhoidal tissue
- temporarily provides a coating for relief of anorectal discomforts
- temporarily protects the inflamed, irritated anorectal surface to help make
bowel movements less painful

Keep out of reach of children. If swallowed, get medical help or contact
a Poison Control Center right away.

Uses
- for temporary relief of pain, soreness and burning
- helps relieve the local itching and discomfort associated with hemorrhoids
- temporarily shrinks hemorrhoidal tissue
- temporarily provides a coating for relief of anorectal discomforts
- temporarily protects the inflamed, irritated anorectal surface to help make
bowel movements less painful
Other information
- store at 20 degrees - 25 degrees C (68 degrees - 77 degrees F)
- for lot number and expiration date, see crimp of tube or see box

Warnings
For external use only.
Ask a doctor before use if you have
- heart disease - high blood pressure - thyroid disease - diabetes
- trouble urinating due to an enlarged prostate gland
Ask a doctor or pharmacist before use if you are presently taking
a prescription drug for high blood pressure or depression
When using this product
- do not exceed the recommended daily dosage unless directed by a doctor
- do not put into rectum by using fingers or any mechanical device or applicator
- use only the provided dispensing cap
Stop use and ask a doctor if
- bleeding occurs
- condition worsens or does not improve within 7 days
- an allergic reaction develops
- the symptom being treated does not subside or if redness, irritation, swelling, pain,
or other symptoms develop or increase
If pregnant or breast feeding, ask a health professional before use.
Keep out of the reach of children.If swallowed, get medical help or contact a Poison Control Center right away

Directions
- adults: when practical, cleanse the affected area by patting or blotting with an
appropriate cleansing wipe. Gently dry by patting or blotting with a tissue or soft
cloth before applying cream.
- When first opening the tube, puncture foil seal with top end of cap.
- apply externally or in the lower portion of the anal canal only
- apply externally to the affected area up to 4 times daily, especially at night,
in the morning or after each bowel movement
- for application in the lower anal canal: remove cover from dispensing cap.
Attach dispensing cap to tube. Lubricate dispensing cap well, then gently
insert cap partway into the anus.
- thoroughly cleanse dispensing cap after each use and replace cover
- children under 12 years of age: ask a doctor

INACTIVE INGREDIENT

Inactive Ingredients aloe barbadensis leaf juice, butylated hydroxyanisole,
cellulose gum, cetyl alcohol, citric acid, disodium EDTA, glyceryl stearate SE,
laureth-23, methylparaben, mineral oil, penthenol, propylene glycol, propyl gallate,
propylparaben, purified water, sodium benzoate, steareth-2, steareth-20,
stearyl alcohol, tocopheryl acetate, xanthan gum